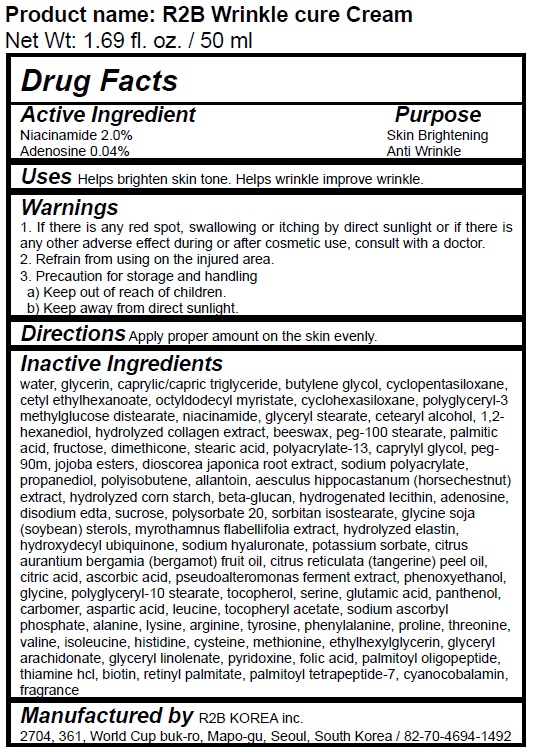 DRUG LABEL: R2B Wrinkle cure Cream
NDC: 73370-0001 | Form: CREAM
Manufacturer: R2B KOREA inc
Category: otc | Type: HUMAN OTC DRUG LABEL
Date: 20191203

ACTIVE INGREDIENTS: NIACINAMIDE 2 g/100 mL; ADENOSINE 0.04 g/100 mL
INACTIVE INGREDIENTS: GLYCERIN; WATER

R2B KOREA inc - R2B Wrinkle cure Cream (2 volume)

ACTIVE INGREDIENT

Niacinamide, Adenosine

INACTIVE INGREDIENT

Water, Glycerin, etc.

PURPOSE

For wrinkle, brightening

keep out of reach of the children

INDICATIONS AND USAGE

Take an appropriate amount of this product and spread it evenly over your skin.

WARNINGS

1. Consult your doctor if you have any abnormal symptoms or side effects such as red spots, swelling or itching due to direct sunlight during or after using cosmetic.
2. Refrain from using the wounded area.
3. Precautions for storage and handling

- Keep out of reach of children
- Store away from direct sunlight

DOSAGE AND ADMINISTRATION

for external use only